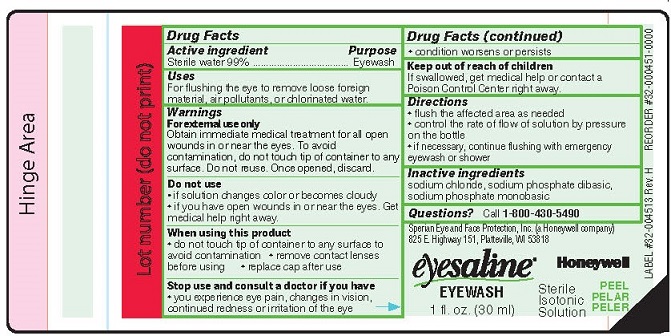 DRUG LABEL: Sperian Eyesaline Eyewash
NDC: 64809-102 | Form: LIQUID
Manufacturer: Sperian Eye & Face Protection Inc
Category: otc | Type: HUMAN OTC DRUG LABEL
Date: 20180618

ACTIVE INGREDIENTS: WATER 99 mL/100 mL
INACTIVE INGREDIENTS: SODIUM PHOSPHATE, DIBASIC; SODIUM CHLORIDE; SODIUM PHOSPHATE, MONOBASIC

Sperian Eyesaline Eyewash

Drug Facts

Active ingredient

Sterile water 99%

Purpose

Eyewash

Uses

For flushing the eye to remove loose foreign material, air pollutants, or chlorinated water.

Warnings

For external use only

Obtain immediate medical treatment for all open wounds in or near the eyes. To avoid contamination, do not touch tip of container to any surface. Do not reuse. Once opened, discard.

Do not use

- if solution changes color or becomes cloudy
- if you have open wounds in or near the eyes. Get medical help right away.

When using this product

- do not touch tip of container to any surface to avoid contamination
- remove contact lenses before using
- replace cap after use

Stop use and consult a doctor if you have

- you experience eye pain, changes in vision, continued redness or irritation of the eye
- condition worsens or persists

Keep out of reach of children. If swallowed, get medical help or contact a Poison Control Center right away.

Directions

- flush the affected eye as needed
- control the rate of flow of the solution by pressure on the bottle
- if necessary, continue flushing with emergency eyewash or shower

Inactive ingredients

sodium chloride, sodium phosphate dibasic, sodium phosphate monobasic

Questions? 1-800 - 430-5490

Sperian Eye and Face Protection, Inc. (a Honeywell Company)

825 E Highway 151
Platteville, WI 53818

PACKAGE LABEL

Honeywell

eyesaline EYEWASH

Sterile Isotonic Solution

1 fl. oz. (30 ml)